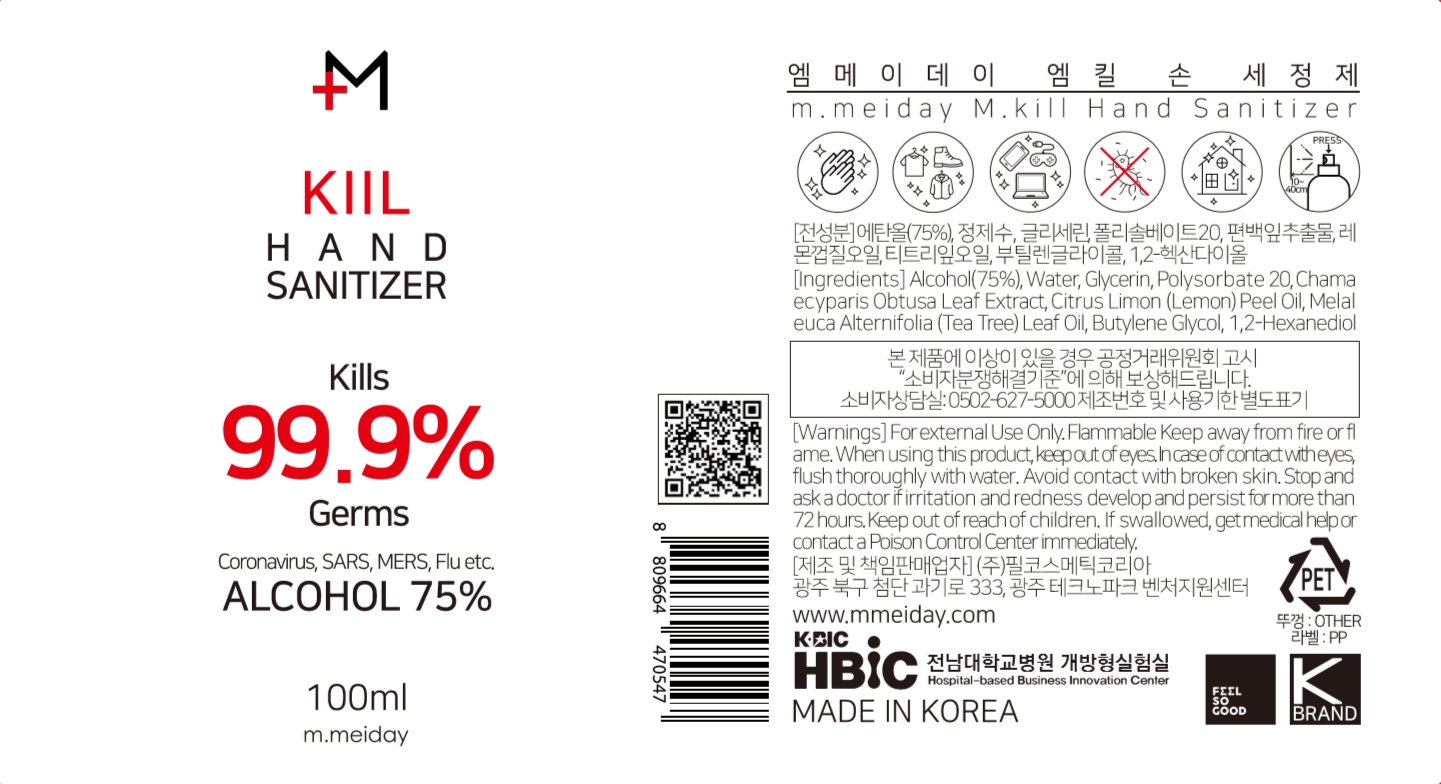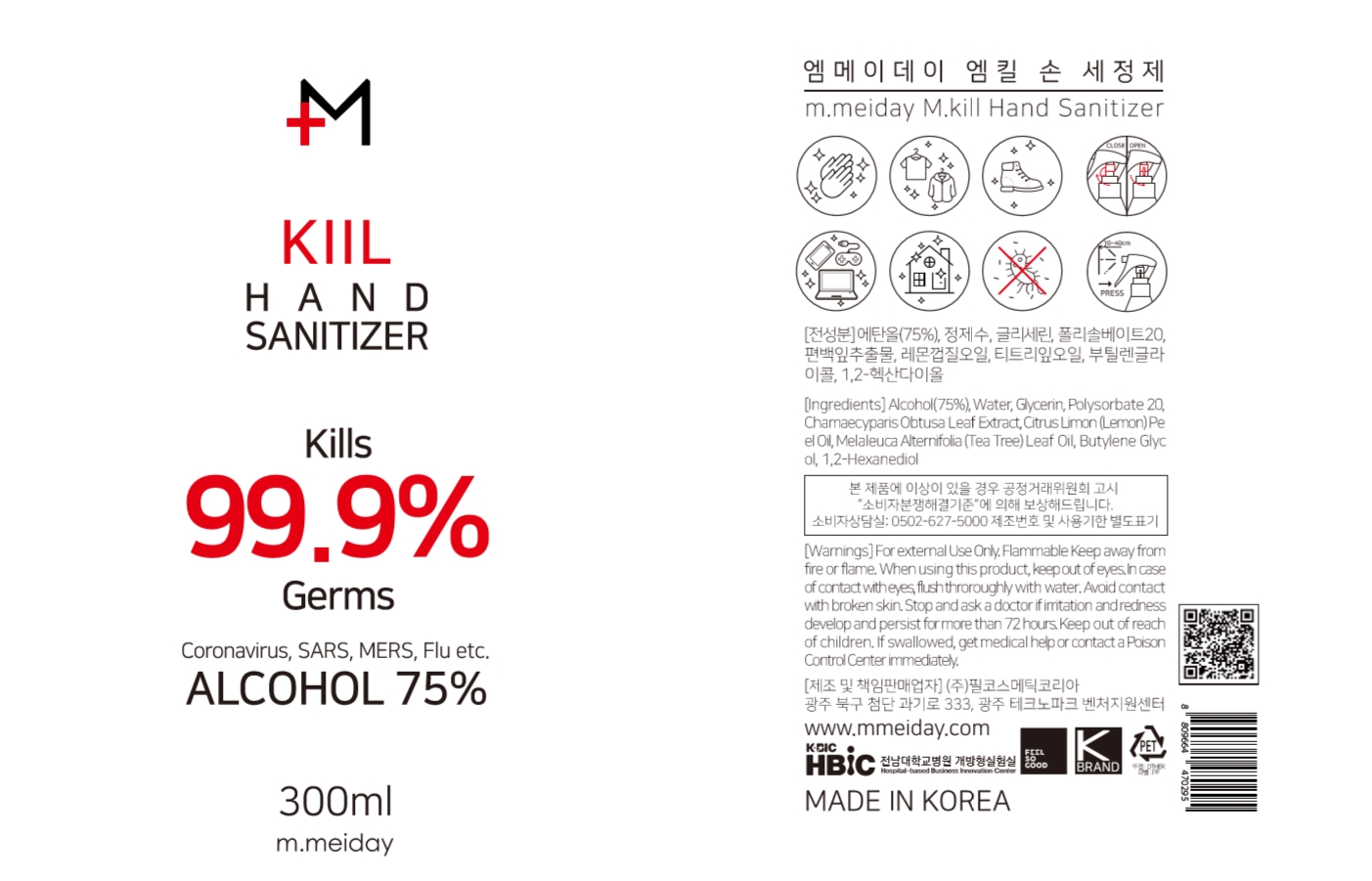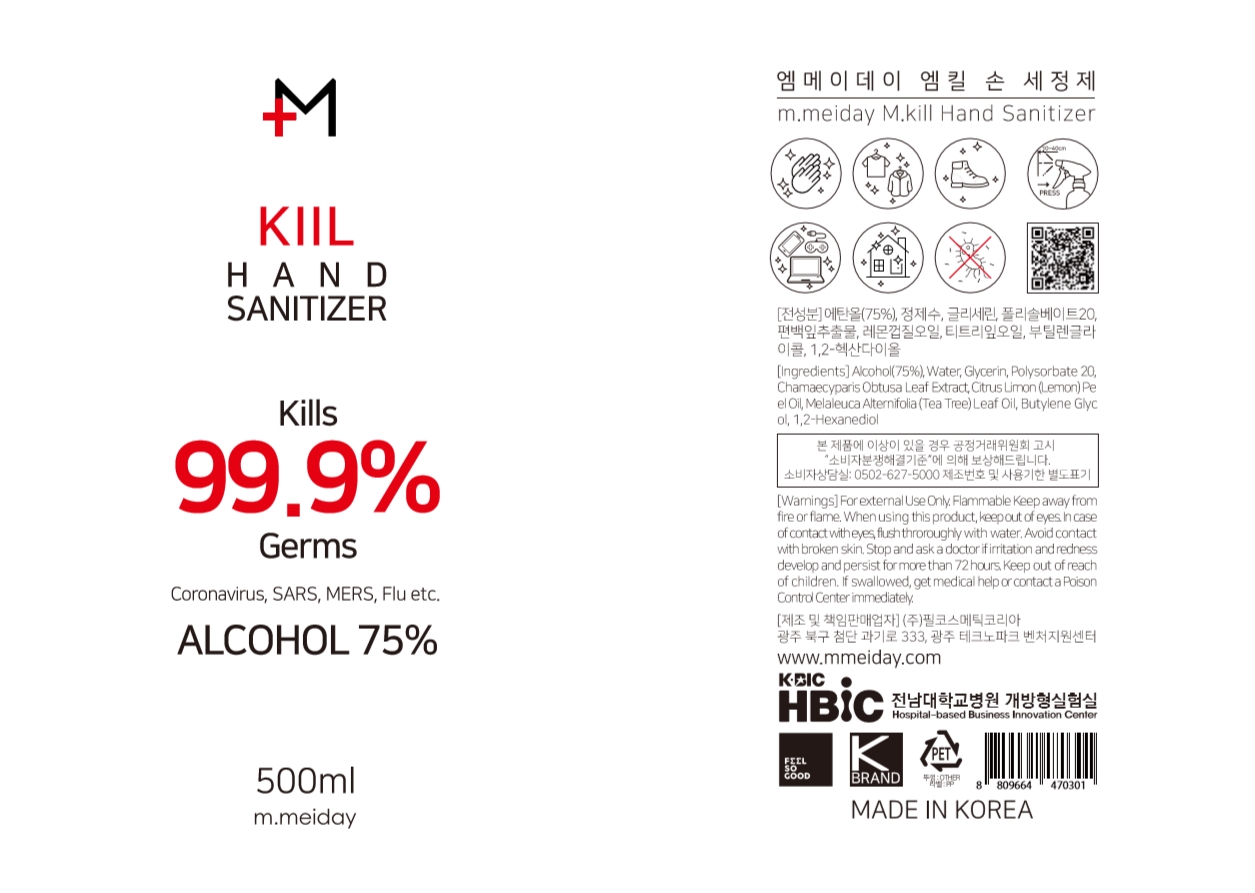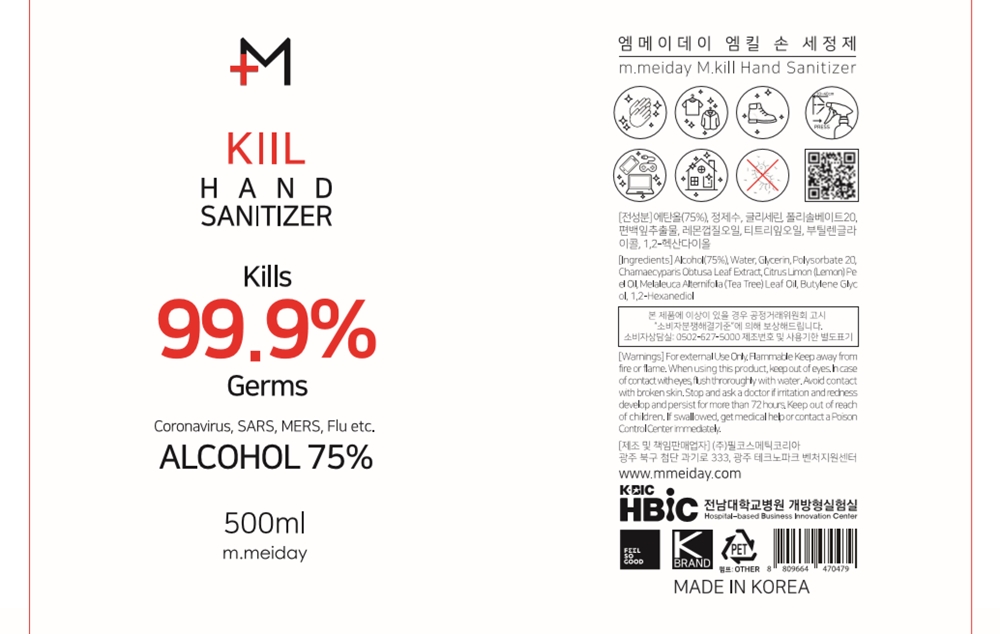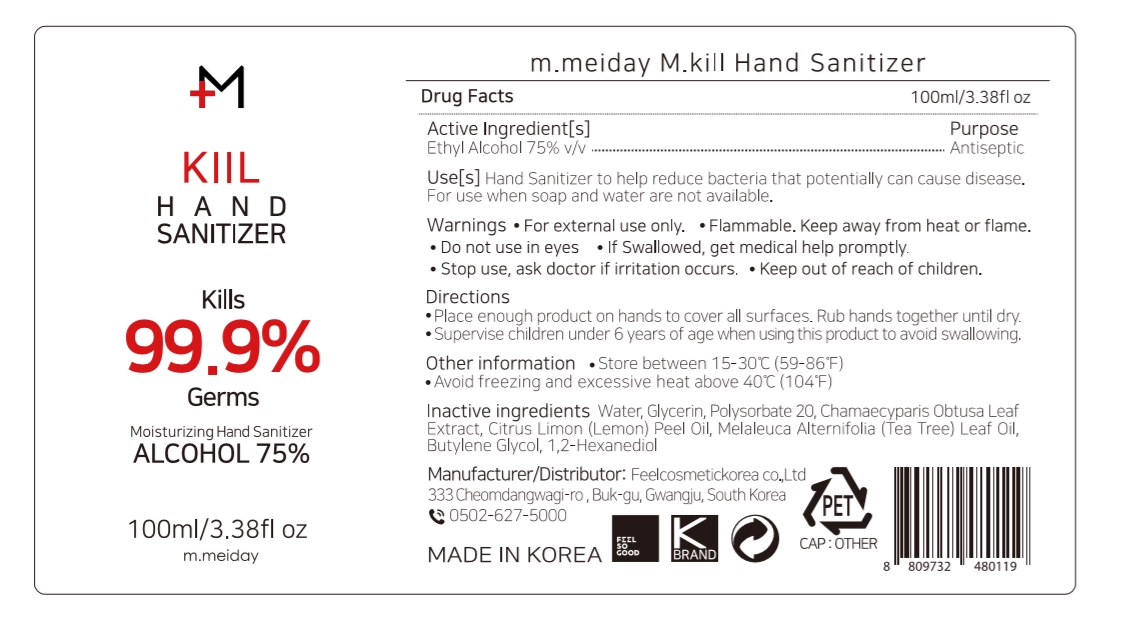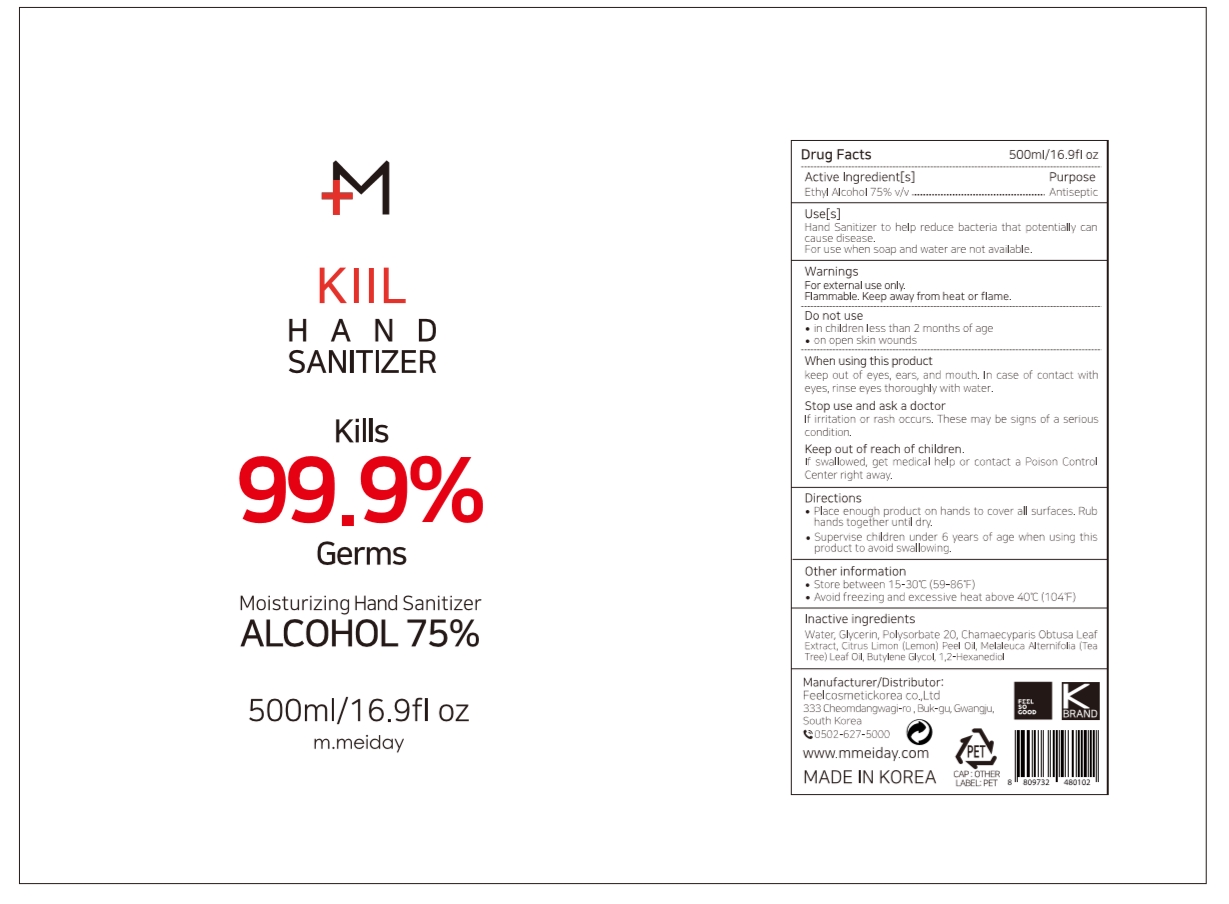 DRUG LABEL: m.meiday M.kill Hand Sanitizer
NDC: 74454-318 | Form: AEROSOL, SPRAY
Manufacturer: FEEL COSMETIC KOREA CO., LTD
Category: otc | Type: HUMAN OTC DRUG LABEL
Date: 20200602

ACTIVE INGREDIENTS: ALCOHOL 75 mL/100 mL
INACTIVE INGREDIENTS: CHAMAECYPARIS OBTUSA LEAF 0.5 mL/100 mL; LEMON OIL 0.1 mL/100 mL; TEA TREE OIL 0.1 mL/100 mL; WATER 21.7 mL/100 mL; 1,2-HEXANEDIOL 0.05 mL/100 mL; GLYCERIN 2 mL/100 mL; BUTYLENE GLYCOL 0.05 mL/100 mL; POLYSORBATE 20 0.5 mL/100 mL

Active Ingredient

Alcohol 75%

Purpose

Antiseptic

Inactive Ingredient

Water, Glycerin, Polysorbate 20, Chama ecyparis Obtusa Leaf Extract, Citrus Limon (Lemon) Peel Oil, Melal euca Alternifolia (Tea Tree) Leaf Oil, Butylene Glycol, 1,2-Hexanediol

Warnings

For external Use Only. Flammable. Keep away from fire or flame.

Warnings

When using this product, keep out of eyes. In case of contact with eyes, flush thoroughly with water.

Warnings

Avoid contact with broken skin.

Warnings

Keep out of reach of children.

Directions

Squeeze a dime-sized drop on hands and rub together. Allow to dry without wiping off.

Use

Hand Sanitizer to help reduce bacteria that potentially can cause disease. For use when soap and water are not available.